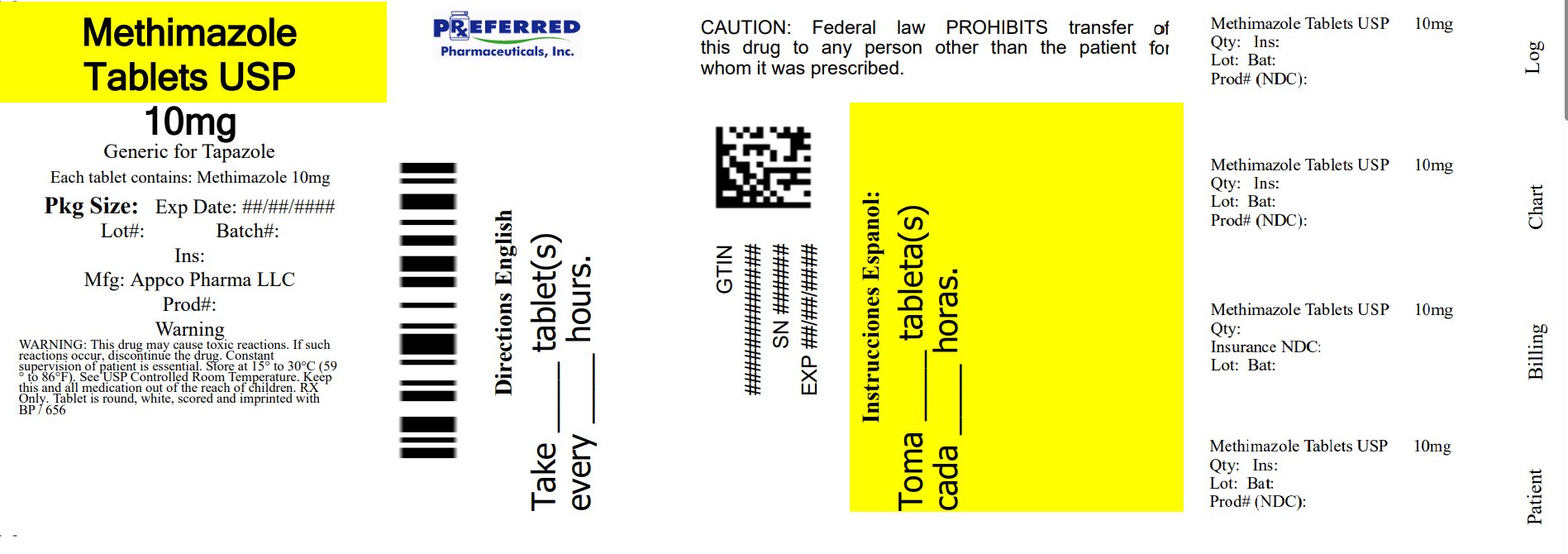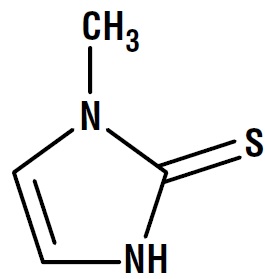 DRUG LABEL: Methimazole
NDC: 68788-4063 | Form: TABLET
Manufacturer: Preferred Pharmaceuticals Inc.
Category: prescription | Type: HUMAN PRESCRIPTION DRUG LABEL
Date: 20260128

ACTIVE INGREDIENTS: METHIMAZOLE 10 mg/1 1
INACTIVE INGREDIENTS: LACTOSE MONOHYDRATE; MAGNESIUM STEARATE; STARCH, CORN

Methimazole Tablets, USP
Rx only

DESCRIPTION

Methimazole, USP (1-methylimidazole-2-thiol) is a white, crystalline substance that is freely soluble in water. It differs chemically from the drugs of the thiouracil series primarily because it has a 5- instead of a 6-membered ring.

Methimazole tablet, USP contains 5 or 10 mg (43.8 or 87.6 μmol) methimazole, an orally administered antithyroid drug.
Each tablet also contains lactose monohydrate, magnesium stearate, and pregelatinized maize starch.

The molecular weight is 114.16, and the molecular formula is C4H6N2S. The structural formula is as follows:

CLINICAL PHARMACOLOGY

Methimazole inhibits the synthesis of thyroid hormones and thus is effective in the treatment of hyperthyroidism. The drug does not inactivate existing thyroxine and tri-iodothyronine that are stored in the thyroid or circulating in the blood nor does it interfere with the effectiveness of thyroid hormones given by mouth or by injection.

Methimazole is readily absorbed in the gastrointestinal tract, metabolized in the liver, and excreted in the urine.

INDICATIONS AND USAGE

Methimazole tablets are indicated:

- In patients with Graves’ disease with hyperthyroidism or toxic multinodular goiter for whom surgery or radioactive iodine therapy is not an appropriate treatment option.
- To ameliorate symptoms of hyperthyroidism in preparation for thyroidectomy or radioactive iodine therapy.

CONTRAINDICATIONS

Methimazole tablets are contraindicated in the presence of hypersensitivity to the drug or any of the other product components.

WARNINGS

First Trimester Use of Methimazole and Congenital Malformations

Methimazole crosses the placental membranes and can cause fetal harm, when administered in the first trimester of pregnancy. Rare instances of congenital defects, including aplasia cutis, craniofacial malformations (facial dysmorphism; choanal atresia), gastrointestinal malformations (esophageal atresia with or without tracheoesophageal fistula), omphalocele and abnormalities of the omphalomesenteric duct have occurred in infants born to mothers who received methimazole tablets in the first trimester of pregnancy. If methimazole tablets are used during pregnancy or if the patient becomes pregnant while taking this drug, the patient should be warned of the potential hazard to the fetus.

Because of the risk for congenital malformations associated with use of methimazole tablets in the first trimester of pregnancy, it may be appropriate to use other agents in pregnant women requiring treatment for hyperthyroidism. If methimazole tablets are used, the lowest possible dose to control the maternal disease should be given.

Agranulocytosis

Agranulocytosis is potentially a life-threatening adverse reaction of methimazole therapy. Patients should be instructed to immediately report to their physicians any symptoms suggestive of agranulocytosis, such as fever or sore throat. Leukopenia, thrombocytopenia, and aplastic anemia (pancytopenia) may also occur. The drug should be discontinued in the presence of agranulocytosis or aplastic anemia (pancytopenia), and the patient's bone marrow indices should be monitored.

Liver Toxicity

Although there have been reports of hepatotoxicity (including acute liver failure) associated with methimazole, the risk of hepatotoxicity appears to be less with methimazole than with propylthiouracil, especially in the pediatric population. Symptoms suggestive of hepatic dysfunction (anorexia, pruritis, right upper quadrant pain, etc.) should prompt evaluation of liver function (bilirubin, alkaline phosphatase) and hepatocellular integrity (ALT, AST). Drug treatment should be discontinued promptly in the event of clinically significant evidence of liver abnormality including hepatic transaminase values exceeding 3 times the upper limit of normal.

Hypothyroidism

Methimazole can cause hypothyroidism necessitating routine monitoring of TSH and free T4 levels with adjustments in dosing to maintain a euthyroid state. Because the drug readily crosses placental membranes, methimazole can cause fetal goiter and cretinism when administered to a pregnant woman. For this reason, it is important that a sufficient, but not excessive, dose be given during pregnancy (see PRECAUTIONS, Pregnancy).

Vasculitis

Cases of vasculitis resulting in severe complications have been reported in patients receiving methimazole therapy. These cases of vasculitis include: leukocytoclastic cutaneous vasculitis, acute kidney injury and glomerulonephritis, alveolar/pulmonary hemorrhage, CNS vasculitis, and neuropathy. Most cases were associated with anti-neutrophilic cytoplasmic antibodies (ANCA)-positive vasculitis. In some cases, vasculitis resolved/improved with drug discontinuation; however, more severe cases required treatment with additional measures including corticosteroids, immunosuppressant therapy, and plasmapheresis. If vasculitis is suspected, discontinue therapy and initiate appropriate intervention.

PRECAUTIONS

General

Patients who receive methimazole should be under close surveillance and should be cautioned to report immediately any evidence of illness, particularly sore throat, skin eruptions, fever, headache, or general malaise. In such cases, white-blood-cell and differential counts should be obtained to determine whether agranulocytosis has developed. Particular care should be exercised with patients who are receiving additional drugs known to cause agranulocytosis.

Information for Patients

Patients should be advised that if they become pregnant or intend to become pregnant while taking an antithyroid drug, they should contact their physician immediately about their therapy.
Inform patients that cases of vasculitis resulting in severe complications have occurred with methimazole tablets. Inform patients to promptly report symptoms that may be associated with vasculitis including new rash, hematuria or decreased urine output, dyspnea or hemoptysis (see WARNINGS and ADVERSE REACTIONS).

Laboratory Tests

Because methimazole may cause hypoprothrombinemia and bleeding, prothrombin time should be monitored during therapy with the drug, especially before surgical procedures. Thyroid function tests should be monitored periodically during therapy. Once clinical evidence of hyperthyroidism has resolved, the finding of a rising serum TSH indicates that a lower maintenance dose of methimazole tablets should be employed.

Drug Interactions

Anticoagulants (oral): Due to potential inhibition of vitamin K activity by methimazole, the activity of oral anticoagulants (e.g., warfarin) may be increased; additional monitoring of PT/INR should be considered, especially before surgical procedures.

β-adrenergic blocking agents: Hyperthyroidism may cause an increased clearance of beta blockers with a high extraction ratio. A dose reduction of beta-adrenergic blockers may be needed when a hyperthyroid patient becomes euthyroid.

Digitalis glycosides: Serum digitalis levels may be increased when hyperthyroid patients on a stable digitalis glycoside regimen become euthyroid; a reduced dosage of digitalis glycosides may be needed.

Theophylline: Theophylline clearance may decrease when hyperthyroid patients on a stable theophylline regimen become euthyroid; a reduced dose of theophylline may be needed.

Carcinogenesis, Mutagenesis, Impairment of Fertility

In a 2 year study, rats were given methimazole at doses of 0.5, 3, and 18 mg/kg/day. These doses were 0.3, 2, and 12 times the 15 mg/day maximum human maintenance dose (when calculated on the basis of surface area). Thyroid hyperplasia, adenoma, and carcinoma developed in rats at the two higher doses. The clinical significance of these findings is unclear.

Pregnancy

See WARNINGS

If methimazole tablets are used during the first trimester of pregnancy or if the patient becomes pregnant while taking this drug, the patient should be warned of the potential hazard to the fetus.

In pregnant women with untreated or inadequately treated Graves’ disease, there is an increased risk of adverse events of maternal heart failure, spontaneous abortion, preterm birth, stillbirth and fetal or neonatal hyperthyroidism.

Because methimazole crosses placental membranes and can induce goiter and cretinism in the developing fetus, hyperthyroidism should be closely monitored in pregnant women and treatment adjusted such that a sufficient, but not excessive, dose be given during pregnancy. In many pregnant women, the thyroid dysfunction diminishes as the pregnancy proceeds; consequently, a reduction of dosage may be possible. In some instances, anti-thyroid therapy can be discontinued several weeks or months before delivery.

Due to the rare occurrence of congenital malformations associated with methimazole use, it may be appropriate to use an alternative anti-thyroid medication in pregnant women requiring treatment for hyperthyroidism particularly in the first trimester of pregnancy during organogenesis.

Given the potential maternal adverse effects of propylthiouracil (e.g., hepatotoxicity), it may be preferable to switch from propylthiouracil to methimazole for the second and third trimesters.

Nursing Mothers

Methimazole is present in breast milk. However, several studies found no effect on clinical status in nursing infants of mothers taking methimazole. A long-term study of 139 thyrotoxic lactating mothers and their infants failed to demonstrate toxicity in infants who are nursed by mothers receiving treatment with methimazole. Monitor thyroid function at frequent (weekly or biweekly) intervals.

Pediatric Use

Because of postmarketing reports of severe liver injury in pediatric patient treated with propylthiouracil, methimazole is the preferred choice when an antithyroid drug is required for a pediatric patient (see DOSAGE AND ADMINISTRATION).

ADVERSE REACTIONS

Major adverse reactions (which occur with much less frequency than the minor adverse reactions) include inhibition of myelopoiesis (agranulocytosis, granulocytopenia, thrombocytopenia, and aplastic anemia), drug fever, a lupus-like syndrome, insulin autoimmune syndrome (which can result in hypoglycemic coma), hepatitis (jaundice may persist for several weeks after discontinuation of the drug), periarteritis, and hypoprothrombinemia. Nephritis occurs very rarely. There have been postmarketing case reports of acute pancreatitis.

There are reports of a vasculitis, often associated with the presence of anti-neutrophilic cytoplasmic antibodies (ANCA), resulting in severe complications (see WARNINGS). Minor adverse reactions include skin rash, urticaria, nausea, vomiting, epigastric distress, arthralgia, paresthesia, loss of taste, abnormal loss of hair, myalgia, headache, pruritus, drowsiness, neuritis, edema, vertigo, skin pigmentation, jaundice, sialadenopathy, and lymphadenopathy.
To report SUSPECTED ADVERSE REACTIONS, contact Rising Pharma Holdings, Inc. at 1-844-874-7464 or FDA at 1-800-FDA-1088 or www.fda.gov/medwatch.

OVERDOSAGE

Signs and Symptoms

Symptoms may include nausea, vomiting, epigastric distress, headache, fever, joint pain, pruritus, and edema. Aplastic anemia (pancytopenia) or agranulocytosis may be manifested in hours to days. Less frequent events are hepatitis, nephrotic syndrome, exfoliative dermatitis, neuropathies, and CNS stimulation or depression. No information is available on the median lethal dose of the drug or the concentration of methimazole in biologic fluids associated with toxicity and/or death.

Treatment

To obtain up-to-date information about the treatment of overdose, a good resource is your certified Regional Poison Control Center. In managing overdosage, consider the possibility of multiple drug overdoses, interaction among drugs, and unusual drug kinetics in the patient.

In the event of an overdose, appropriate supportive treatment should be initiated as dictated by the patient’s medical status.

DOSAGE AND ADMINISTRATION

Methimazole tablets are administered orally. The total daily dosage is usually given in 3 divided doses at approximately 8-hour intervals.

Adult - The initial daily dosage is 15 mg for mild hyperthyroidism, 30 to 40 mg for moderately severe hyperthyroidism, and 60 mg for severe hyperthyroidism, divided into 3 doses at 8-hour intervals. The maintenance dosage is 5 to 15 mg daily.

Pediatric - Initially, the daily dosage is 0.4 mg/kg of body weight divided into 3 doses and given at 8-hour intervals. The maintenance dosage is approximately 1/2 of the initial dose.

HOW SUPPLIED

Methimazole tablets, USP are available in:

Methimazole Tablets, USP 10 mg - White to off-white, round tablets debossed with "656" on one side and "B/P" on the other side.

Bottles of 30 NDC 68788-4063-3

Bottles of 100 NDC 68788-4063-1

STORAGE

Store at 20° to 25°C (68° to 77°F); excursions permitted between 15° to 30°C (59° to 86°F) [See USP Controlled Room Temperature].

Dispense in tight, light-resistant container.

Manufactured by:

Appco Pharma LLC

Piscataway, NJ 08854

Manufactured for:

Rising Pharma Holdings, Inc.

East Brunswick, NJ 08816

Revised: 02/2025
200681
PIR26501-01

Repackaged By: Preferred Pharmaceuticals Inc.

PACKAGE LABEL.PRINCIPAL DISPLAY PANEL

PRINCIPAL DISPLAY PANEL - 10 mg
NDC 68788-4063